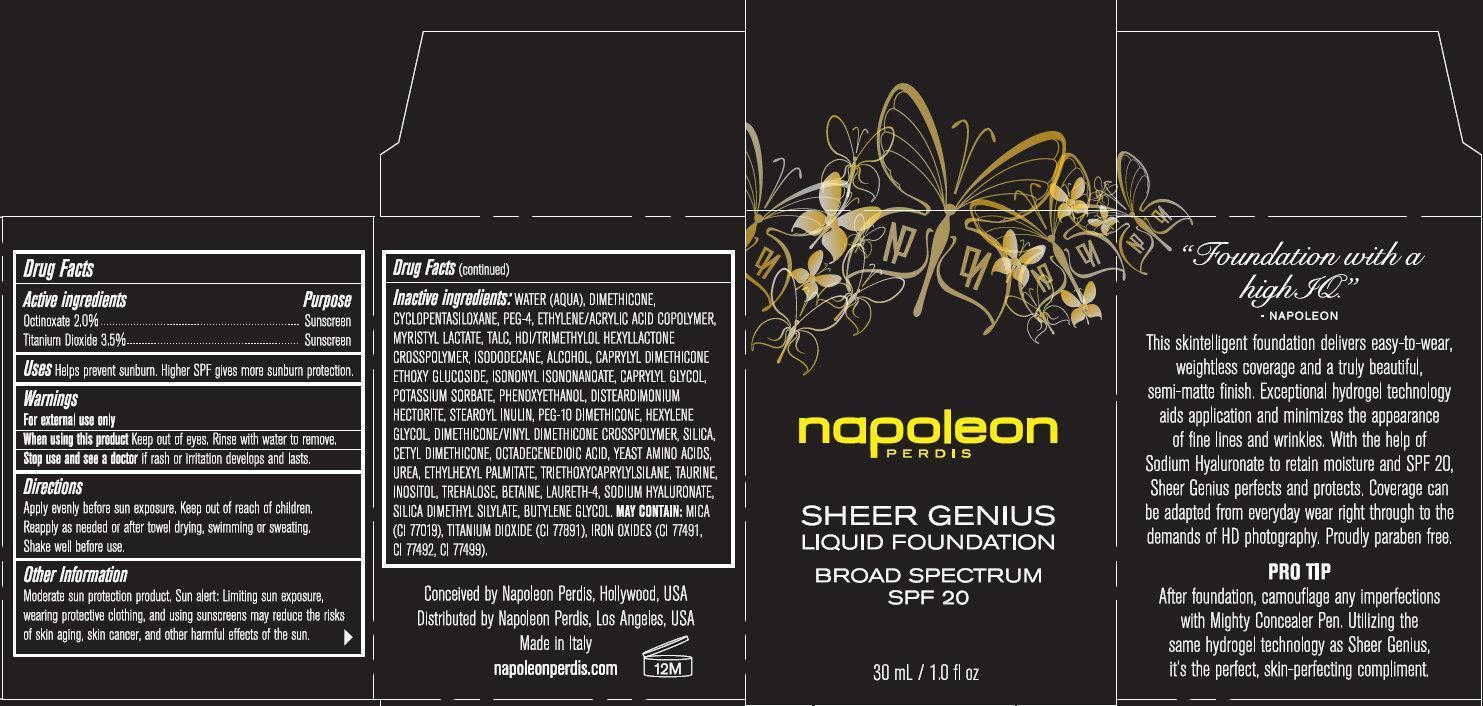 DRUG LABEL: napoleon PERDIS SHEER GENIUS LIQUID FOUNDATION BROAD SPECTRUM SPF 20 Look 6
NDC: 51386-726 | Form: LIQUID
Manufacturer: Napoleon Perdis Cosmetics, Inc
Category: otc | Type: HUMAN OTC DRUG LABEL
Date: 20131212

ACTIVE INGREDIENTS: OCTINOXATE 20 mg/1 mL; TITANIUM DIOXIDE 35 mg/1 mL
INACTIVE INGREDIENTS: WATER; DIMETHICONE; CYCLOMETHICONE 5; POLYETHYLENE GLYCOL 200; ETHYLENE; MYRISTYL LACTATE; TALC; HEXAMETHYLENE DIISOCYANATE; ISODODECANE; ALCOHOL; ISONONYL ISONONANOATE; CAPRYLYL GLYCOL; POTASSIUM SORBATE; PHENOXYETHANOL; DISTEARDIMONIUM HECTORITE; HEXYLENE GLYCOL; SILICON DIOXIDE; OCTADECENEDIOIC ACID; UREA; ETHYLHEXYL PALMITATE; TRIETHOXYCAPRYLYLSILANE; TAURINE; INOSITOL; TREHALOSE; BETAINE; LAURETH-4; HYALURONATE SODIUM; SILICA DIMETHYL SILYLATE; BUTYLENE GLYCOL; MICA; FERRIC OXIDE RED; FERRIC OXIDE YELLOW; FERROSOFERRIC OXIDE

napoleon PERDIS SHEER GENIUS LIQUID FOUNDATION BROAD SPECTRUM SPF 20 Look 6

Active ingredients

Octinoxate 2.0%
Titanium Dioxide 3.5%

Purpose

Sunscreen

Uses

Helps prevent sunburn. Higher SPF gives more sunburn protection.

Warnings

For external use only.

When using this product:

keep out of eyes. Rinse with water to remove.

Stop use and see a doctor

if rash or irritation develops and lasts.

Directions

Apply evenly before sun exposure. Children under 6 months of age: ask a doctor. Reapply as needed or after towel drying, swimming or sweating.

Other Information

Moderate sun protection product. Sun alert: Limiting sun exposure, wearing protective clothing, and using sunscreens may reduce the risks of skin aging, skin cancer, and other harmful effects of the sun.

Inactive ingredients:

WATER, (AQUA), DIMETHICONE, CYCLOPENTASILOXANE, PEG-4, ETHYLENE/ACRYLIC ACID COPOLYMER, MYRISTYL LACTATE, TALC, HDI/TRIMETHYLOL HEXYLLACTONE CROSSPOLYMER, ISODODECANE, ALCOHOL, CAPRYLYL DIMETHICONE ETHOXY GLUCOSIDE, ISONONYL ISONONANOATE, CAPRYLYL GLYCOL, POTASSIUM SORBATE, PHENOXYETHANOL, DISTEARDIMONIUM HECTORITE, STEAROYL INULIN, PEG-10 DIMETHICONE, HEXYLENE GLYCOL, DIMETHICONE/VINYL DIMETHICONE CROSSPOLYMER, SILICA, CETYL DIMETHICONE, OCTADECENEDIOIC ACID, YEAST AMINO ACIDS, UREA, ETHYLHEXYL PALMITATE, TRIETHOXYCAPRYLYLSILANE, TAURINE, INOSITOL, TREHALOSE, BETAINE, LAURETH-4, SODIUM HYALURONATE, SILICA DIMETHYL SILYLATE, BUTYLENE GLYCOL. MAY CONTAIN: MICA (CI 77019), TITANIUM DIOXIDE (CI 77891), IRON OXIDES (CI 77491, CI 77492, CI 77499).